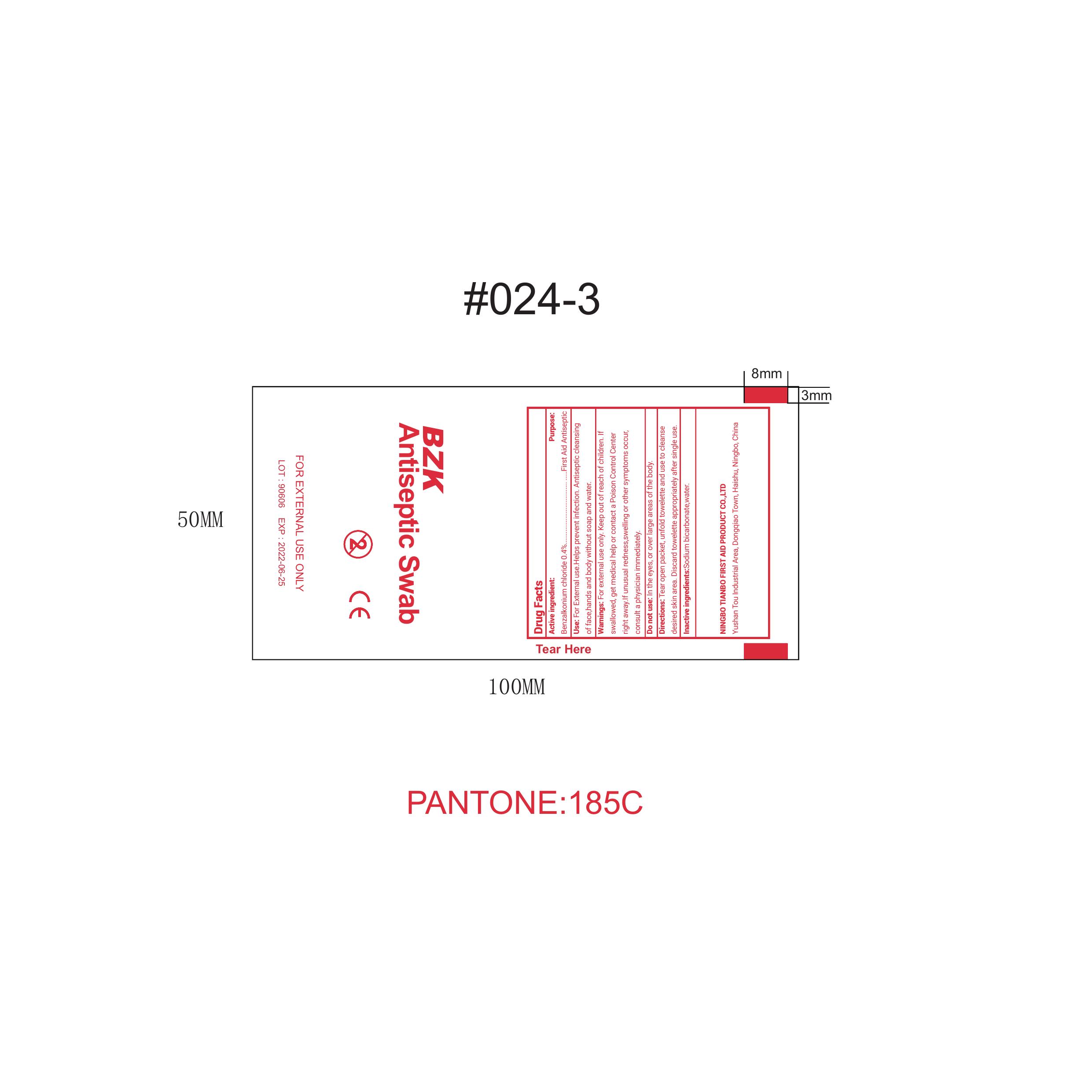 DRUG LABEL: BZK Antiseptic Swab
NDC: 73288-003 | Form: SOLUTION
Manufacturer: NINGBO TIANBO FIRST AID PRODUCT CO., LTD.
Category: otc | Type: HUMAN OTC DRUG LABEL
Date: 20260112

ACTIVE INGREDIENTS: BENZALKONIUM CHLORIDE 0.4 g/100 mL
INACTIVE INGREDIENTS: SODIUM BICARBONATE; WATER

73288-003

Active Ingredient: Benzalkonium Chloride 0.4%

Purpose: First Aide Antiseptic

INDICATIONS AND USAGE

Uses: For external use. Help prevent infection. Antiseptic cleasing of face, hand, and body withour soap and water.

Warnings:

For external use only

Keep out of reach of children. If swallowed, get medical help or contact a Poison Control Center right away. If usual redness, swelling, or other symptoms occur, consult a physician immediately.

DOSAGE AND ADMINISTRATION

Directions: Tear open packet, unfold towelette and use to clease desire skin area. Discard towelette appropriately after single use.

Do not use in the eyes or over large area of the body.

Inactive Ingredient

Sodium Bicarbonate, Water